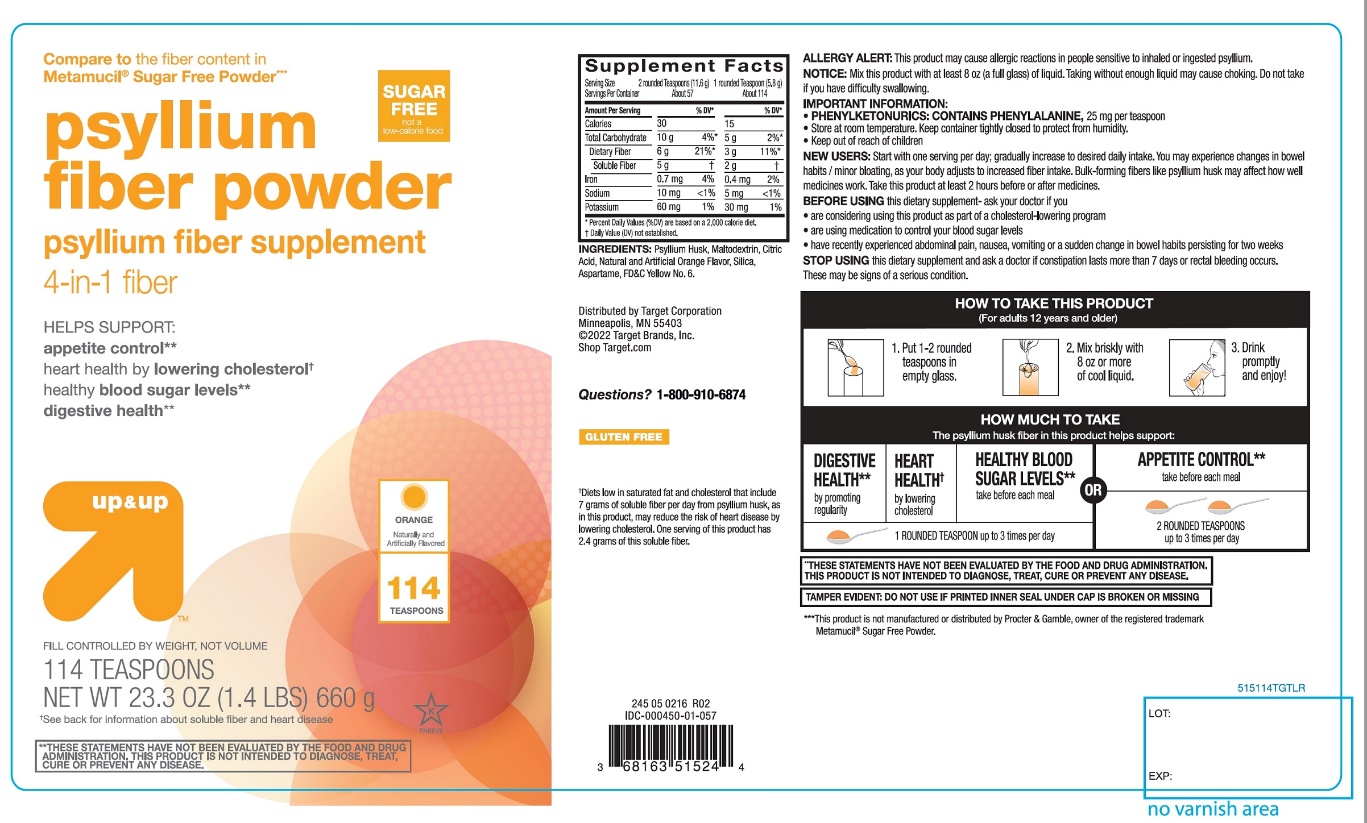 DRUG LABEL: up and up fiber therapy
NDC: 11673-669 | Form: POWDER
Manufacturer: Target Corporation
Category: otc | Type: HUMAN OTC DRUG LABEL
Date: 20251105

ACTIVE INGREDIENTS: PSYLLIUM HUSK 3.4 g/5.79 g
INACTIVE INGREDIENTS: ASPARTAME; CITRIC ACID MONOHYDRATE; FD&C YELLOW NO. 6; MALTODEXTRIN; SILICON DIOXIDE

up and up fiber therapy 100% natural psyllium husk

Drug Facts

Active ingredient: (in each TEASPOON)

Psyllium husk approximately 3.4 g

Purpose

Fiber therapy for regularity

Uses:

- for relief of occasional constipation (irregularity)

Warnings:

Choking

Taking this product without adequate fluid may cause it to swell and block your throat or esophagus and may cause choking. Do not take this product if you have difficulty in swallowing. If you experience chest pain, vomiting, or difficulty in swallowing or breathing after taking this product, seek immediate medical attention.

Allergy alert:

This product may cause allergic reaction in people sensitive to inhaled or ingested psyllium.

Ask a doctor before use if you have

- a sudden change in bowel habits persisting for 2 weeks
- abdominal pain, nausea or vomiting

Stop use and ask a doctor if

- constipation lasts more than 7 days
- rectal bleeding occurs

These may be signs of a serious condition.

Keep out of reach of children.In case of overdose, get medical help or contact a Poison Control Center right away at 1-800-222-1222.

Directions:

Put one dose into an empty glass. Mix this product (child or adult dose) with at least 8 ounces (a full glass) of water or other fluid. Taking this product without enough liquid may cause choking. See choking warning. Stir briskly and drink promptly. If mixture thickens, add more liquid and stir.

Adults 12 years & older: | 1 rounded TEASPOON in 8 oz of liquid at the first sign of irregularity. Can be taken up to 3 times daily. Generally produces effect in 12 – 72 hours.
Children 6 – 11 yrs : | ½ adult dose in 8 oz of liquid, up to 3 times daily
Children under 6 yrs: | Consult a doctor

Bulk forming fibers like psyllium husk may affect how well other medicines work. If you are taking a prescription medicine by mouth, take this product at least 2 hours before or 2 hours after the prescribed medicine. As your body adjusts to increased fiber intake, you may experience changes in bowel habits or minor bloating.

New Users

Start with 1 serving per day; gradually increased to desired daily intake. You may initially experience changes in bowel habits or minor bloating, as your body adjusts to increased fiber intake.

Other information:

- each teaspoon contains:potassium 35 mg; sodium 5 mg
- PHENYLKETONURICS: CONTAINS PHENYLALANINE,25 mg per teaspoon
- store at room temperature tightly closed to protect from humidity
- do not use if printed inner seal is broken or missing
- contains a 100% natural, therapeutic fiber

Inactive ingredients:

aspartame, citric acid, FD&C yellow 6, maltodextrin, natural and artificial orange flavor, silica.

Questions or comments?

Call 1-800-910-6874

PRINCIPAL DISPLAY PANEL

NDC 11673-669-91

Compare to active ingredient in Metamucil® 4 in 1 MultiHealth Fiber***

fiber therapy

100% natural psyllium husk

multi-benefit daily fiber supplement therapy for regularity

helps you feel less hungry between meals**

helps maintain healthy blood sugarlevels as part of your diet **

helps lower cholesterolto promote heart health†

promotes digestive health**

sugar free

not a low calorie food

ORANGEFLAVOR 114 DOSES‡

FILL CONTROLLED BY WEIGHT NOT VOLUME

114 TEASPOON DOSES‡

NET WT 23.3 OZ (1.4 LB) 660 g

Naturally and Artificially Flavored

245 05 0216 R01 ID295403

Distributed by Target Corporation

Minneapolis, MN 55403

©2015 Target Brands, Inc.

Shop Target.com

GLUTEN FREE

**These statements have not been evaluated by the Food and Drug Administration. This product is not intended to diagnose, treat, cure or prevent any disease.

†See back for information about soluble fiber and heart disease

‡Serving size varies. See DIRECTIONS on back panel for more information

This product has a low glycemic index, a measure of the effect of dietary carbohydrates on blood sugar levels.

100% satisfaction guaranteed or your money back.

***This product is not manufactured or distributed by Procter & Gamble, owner of the registered trademark Metamucil ®.